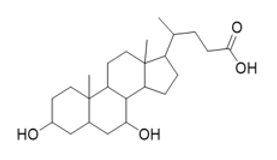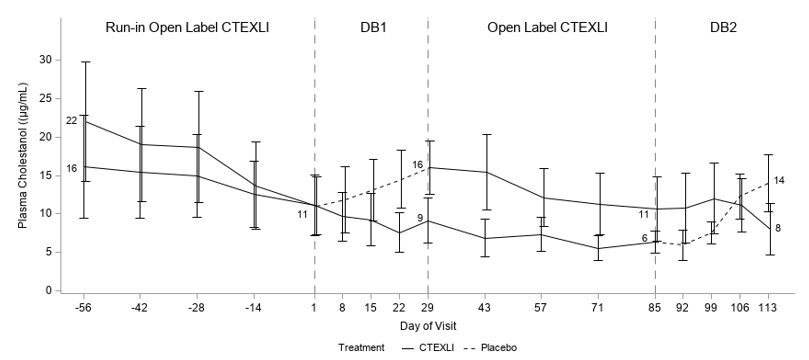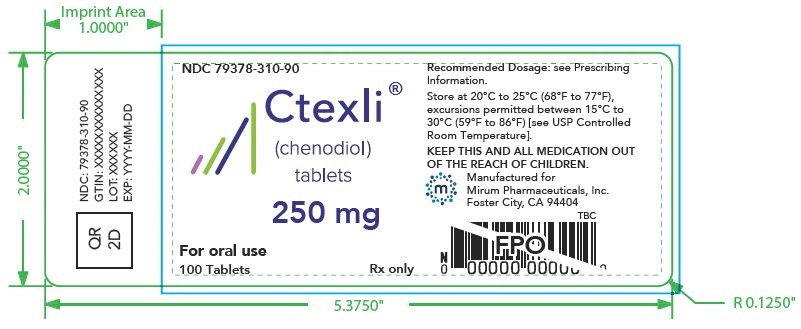 DRUG LABEL: CTEXLI
NDC: 79378-310 | Form: TABLET, FILM COATED
Manufacturer: Mirum Pharmaceuticals Inc.
Category: prescription | Type: HUMAN PRESCRIPTION DRUG LABEL
Date: 20251216

ACTIVE INGREDIENTS: CHENODIOL 250 mg/1 1
INACTIVE INGREDIENTS: SILICON DIOXIDE; MICROCRYSTALLINE CELLULOSE; SODIUM STARCH GLYCOLATE TYPE A POTATO; MAGNESIUM STEARATE; METHYLCELLULOSE (100 MPA.S); GLYCERIN; SODIUM LAURYL SULFATE; STARCH, CORN

HIGHLIGHTS OF PRESCRIBING INFORMATION

These highlights do not include all the information needed to use CTEXLI safely and effectively. See full prescribing information for CTEXLI.
CTEXLI® (chenodiol) tablets, for oral use
Initial U.S. Approval: 1983

1 INDICATIONS AND USAGE

CTEXLI is a bile acid indicated for treatment of cerebrotendinous xanthomatosis (CTX) in adults. (1)

2 DOSAGE AND ADMINISTRATION

- Before initiating CTEXLI, obtain baseline liver transaminase (alanine aminotransferase [ALT] and aspartate aminotransferase [AST]) and total bilirubin levels in all patients. (2.1)
- The recommended dosage is 250 mg orally three times daily. (2.2)

3 DOSAGE FORMS AND STRENGTHS

CTEXLI tablets: 250 mg. (3)

4 CONTRAINDICATIONS

None. (4)

5 WARNINGS AND PRECAUTIONS

Hepatotoxicity: Obtain baseline liver transaminase and total bilirubin levels in all patients and monitor yearly and as clinically indicated. Interrupt treatment until the levels have returned to baseline values. For persistent or recurrent liver test abnormalities, consider discontinuing CTEXLI. (5.1)

6 ADVERSE REACTIONS

The most common adverse reactions (incidence > 14%) are diarrhea, headache, abdominal pain, constipation, hypertension, muscular weakness, and upper respiratory tract infection. (6.1)

To report SUSPECTED ADVERSE REACTIONS, contact Mirum Pharmaceuticals at 1-855-MRM-4YOU or FDA at 1-800-FDA-1088 or www.fda.gov/medwatch.

7 DRUG INTERACTIONS

- Bile acid sequestering agents and aluminum-based antacids: Avoid concomitant use with CTEXLI. (7.1)
- Coumarin and its derivatives: Monitor prothrombin time and adjust dosage accordingly. (7.2)

FULL PRESCRIBING INFORMATION

1 INDICATIONS AND USAGE

CTEXLI is indicated for the treatment of cerebrotendinous xanthomatosis (CTX) in adults.

2 DOSAGE AND ADMINISTRATION

2.1 Important Recommendation Prior to CTEXLI Treatment Initiation

Before initiating CTEXLI, obtain baseline liver transaminase (alanine aminotransferase [ALT] and aspartate aminotransferase [AST]) and total bilirubin levels in all patients [see Warnings and Precautions (5.1)].

2.2 Recommended Dosage

The recommended dosage of CTEXLI is 250 mg administered orally three times daily.

Administer CTEXLI with or without food. Swallow tablets whole.

Missed Dose

If a dose of CTEXLI is missed, advise the patient to skip the missed dose and to resume taking the prescribed dose at the next scheduled time. Patients should not take a double dose.

2.3 Administration Modification and Monitoring

If liver transaminase (ALT, AST) levels are elevated > 3 times the upper limit of normal (ULN) or total bilirubin level is >2 times ULN, interrupt treatment with CTEXLI until the levels have returned to baseline values. Monitor liver transaminase and total bilirubin levels yearly and as clinically indicated [see Warnings and Precautions (5.1)].

3 DOSAGE FORMS AND STRENGTHS

Tablets: 250 mg of chenodiol as white film-coated tablets imprinted with “MP” on one side and "250" on the other side.

4 CONTRAINDICATIONS

None.

5 WARNINGS AND PRECAUTIONS

5.1 Hepatotoxicity

Chenodiol, including CTEXLI, has been associated with hepatotoxicity [see Adverse Reactions (6)]. In Trial 1, one CTEXLI-treated patient (7%) had increased ALT levels > 3 times ULN, which led to treatment interruption. Patients with pre-existing liver disease or bile duct abnormalities may be at higher risk for hepatotoxicity during treatment with CTEXLI. Published reports suggest patients who are poor sulfators of lithocholic acid are more likely to develop chenodiol-induced serum aminotransferase elevations [see Clinical Pharmacology (12.3)].

Obtain baseline liver transaminase (ALT, AST) and total bilirubin levels in all patients prior to treatment initiation with CTEXLI. If liver transaminase levels are elevated > 3 times ULN or total bilirubin level is >2 times ULN, interrupt treatment with CTEXLI until the levels have returned to baseline values. Monitor liver transaminase and total bilirubin levels yearly and as clinically indicated. For persistent or recurrent liver test abnormalities, consider discontinuing CTEXLI.

Inform the patient of the symptoms of hepatotoxicity (e.g., abdominal pain, bruising, dark-colored urine, fatigue, bleeding, jaundice, nausea, and pruritus). If clinical signs and symptoms consistent with hepatotoxicity occur, have the patient discontinue CTEXLI immediately.

6 ADVERSE REACTIONS

The following clinically significant adverse reaction is described elsewhere in the labeling:

- Hepatotoxicity [see Warnings and Precautions (5.1)]

6.1 Clinical Trials Experience

Because clinical trials are conducted under widely varying conditions, adverse reaction rates observed in the clinical trials of a drug cannot be directly compared to rates in the clinical trials of another drug and may not reflect the rates observed in practice.

The safety of CTEXLI was evaluated in a randomized, double blind, placebo-controlled, 2-period, 2-treatment crossover trial in 14 patients (16 to 55 years of age) with CTX (Trial 1). CTEXLI is not approved for use in pediatric patients. The dosage of CTEXLI was 250 mg orally three times a day [see Clinical Studies (14)]. The mean (SD) chenodiol exposure during Trial 1 was 139.1 (26.7) days.

The most common adverse reactions which occurred in two or more patients (>14%) during CTEXLI treatment (including the two 8-week open-label treatment periods) were diarrhea (36%), headache (21%), and abdominal pain (including abdominal pain upper) (14%), constipation (14%), hypertension (14%), muscular weakness (14%), and upper respiratory tract infection (14%).

In Trial 1, one CTEXLI-treated patient (7%) had increased ALT levels > 3x ULN, which led to treatment interruption.

6.2 Postmarketing Experience

The following adverse reactions have been identified during post approval use of chenodiol. Because these reactions are reported voluntarily from a population of uncertain size, it is not always possible to reliably estimate their frequency or establish a causal relationship to drug exposure.

- Hepatobiliary Disorders: Hepatotoxicity [see Warnings and Precautions (5.1)]
- Immune System Disorders: Hypersensitivity reactions such as facial swelling, pruritus, rash, urticaria.

7 DRUG INTERACTIONS

7.1 Effect of Other Drugs on CTEXLI

Co-administration of bile acid sequestering agents, such as cholestyramine and colestipol, or aluminum-based antacids may decrease absorption of CTEXLI in the intestine and may result in decreased efficacy of CTEXLI. Avoid concomitant use of bile acid sequestering agents or aluminum-based antacids with CTEXLI.

7.2 Effect of CTEXLI on Other Drugs

Due to potential hepatotoxicity, CTEXLI may affect the pharmacodynamics of coumarin and its derivatives, causing unexpected prolongation of the prothrombin time and hemorrhage. If concomitant use of CTEXLI with coumarin or its derivatives is unavoidable, monitor prothrombin time. Adjust the dosage of coumarin or its derivatives in accordance with its approved product labeling.

8 USE IN SPECIFIC POPULATIONS

8.1 Pregnancy

Risk Summary

Available data from published case reports over decades of use with chenodiol during pregnancy have not identified an increased risk of major birth defects, miscarriage, or other adverse maternal or fetal outcomes. Serious hepatic, renal and adrenal lesions occurred in fetuses of female Rhesus monkeys treated at doses 1 to 2 times the recommended human dose based on body surface area (mg/m^2). Hepatic lesions also occurred at doses comparable to the human dose based on body surface area in neonatal baboons born to mothers administered chenodiol during pregnancy (see Data). The animal study findings have not been demonstrated with human use.

The background risk of major birth defects and miscarriage for the indicated population is unknown. All pregnancies have a background risk of birth defect, loss, or other adverse outcomes. In the US general population, the estimated background risk of major birth defects and miscarriage in clinically recognized pregnancies is 2 to 4% and 15 to 20%, respectively.

Data

Animal Data

Hepatic lesions were reported in neonatal baboons whose mothers had received 18 to 38 mg/kg of chenodiol throughout pregnancy (0.6 to 1.4 times the recommended human dose based on body surface area). Serious hepatic, renal and adrenal lesions were also reported in fetuses of female Rhesus monkeys given 60 to 90 mg/kg/day from GD 21-45 of pregnancy (1 to 2 times the recommended human dose based on body surface area). Non-human primates form sulfate conjugates of the known hepatotoxic bacterial metabolite of chenodiol, lithocholic acid, to a lesser extent than reported in humans, which may exaggerate the toxicity of orally dosed chenodiol compared to humans. However, there is also evidence that the hepatobiliary toxicity is partly due to the parent drug, chenodiol.

8.2 Lactation

Risk Summary

There are no data on the presence of chenodiol in either human or animal milk, the effects on the breastfed infant, or the effects on milk production. The developmental and health benefits of breastfeeding should be considered along with the mother’s clinical need for CTEXLI and any potential adverse effects on the breastfed infant from CTEXLI or the underlying maternal condition.

8.4 Pediatric Use

The safety and effectiveness of CTEXLI for the treatment of CTX have not been established in pediatric patients.

8.5 Geriatric Use

Trial 1 of CTEXLI in patients with CTX did not include patients aged 65 years and older.

10 OVERDOSAGE

Cases of intentional overdose with chenodiol have been reported: one patient consumed 3 g to 4.5 g of chenodiol and another patient consumed 30 g of chenodiol. Clinical manifestations experienced by these patients included nausea, dizziness, and diarrhea.

In the event of an overdose, discontinue CTEXLI, monitor the patient, and institute general supportive measures if needed.

11 DESCRIPTION

CTEXLI (chenodiol) is a bile acid. Chenodiol is a bitter-tasting, white powder consisting of crystalline and amorphous particles that are freely soluble in methanol, acetone and acetic acid, and practically insoluble in water.

The chemical name of chenodiol is 3α,7α-dihydroxy-5-β-cholan-24-oic acid. The molecular formula is C24H40O4 and the molecular weight is 392.58 g/mol. The chemical structure is:

Each CTEXLI tablet contains 250 mg of chenodiol. Inactive ingredients are magnesium stearate, microcrystalline cellulose, pregelatinized starch, silicon dioxide, and sodium starch glycolate. The thin-film coating contains opadry YS 2 7035 (consisting of methylcellulose and glycerin) and sodium lauryl sulfate.

12 CLINICAL PHARMACOLOGY

12.1 Mechanism of Action

Endogenous chenodiol (chenodeoxycholic acid) is a primary bile acid, synthesized from cholesterol in the liver. In CTX, the major bile acid synthesis pathways are disrupted due to partial or total deficiency in sterol 27-hydroxylase encoded by the CYP27A1 gene.

CTEXLI may act to replace deficient levels of the endogenous bile acid chenodeoxycholic acid in patients with CTX. Increased chenodiol levels in the enterohepatic bile acid pool restore the activation of farnesoid X receptor (FXR) and downregulate CYP7A1 leading to suppression and reduction of atypical bile acids and bile alcohols including cholestanol and 23S-pentol.

12.2 Pharmacodynamics

In Trial 1, plasma cholestanol and urine 23S-pentol concentrations were elevated in patients with CTX. Treatment with CTEXLI resulted in reductions of plasma cholestanol and urine 23S-pentol concentrations in the 8-week run-in open label treatment period. Continued treatment with CTEXLI for 4 weeks in the double-blind treatment period resulted in the maintenance of low levels of urine 23S-pentol and additional reductions of plasma cholestanol [see Clinical Studies (14)].

12.3 Pharmacokinetics

In CTX patients, the geometric mean (%CV) maximum plasma concentration (Cmax), trough plasma concentration (Ctrough), and area under the plasma concentration-time curve (AUC0-8h) of chenodiol at steady state following the recommended dosage (250 mg administered orally three times daily) were 3.7 mcg/mL (60%), 0.7 mcg/mL (90%), and 12.5 mcg*h/mL (60%), respectively.

Absorption

The median (range) Tmax of chenodiol following an oral administration in CTX patients was 3 (0.5‑8) hours.

Distribution

Due to first-pass hepatic clearance, the body pool of chenodiol resides mainly in the enterohepatic circulation. The apparent volume of distribution of chenodiol at steady-state was 0.36 L/kg. The plasma protein binding of chenodiol was approximately 98%.

Elimination

The geometric mean total apparent clearance of chenodiol in CTX patients was 20 L/h.

Metabolism

Chenodiol is well absorbed from the small intestine and taken up by the liver where it is converted to its taurine and glycine conjugates and secreted into the bile along with other endogenous bile acids in the enterohepatic circulation. Chenodiol that escapes to the colon is converted by bacterial action to lithocholic acid. Humans have the capacity to form sulfate conjugates of lithocholic acid. About 80% of the lithocholate is excreted in the feces and the remainder is absorbed and converted in the liver to its poorly absorbed sulfolithocholyl conjugates.

Excretion

Conjugated chenodiol is either reabsorbed in the terminal ileum, deconjugated before excretion, or decomposed by bacteria to lithocholic acid.

Drug Interaction Studies

Based on in vitro studies, chenodiol and its glyco- and tauro- conjugates are not expected to inhibit CYPs 1A2, 2B6, 2C8, 2C9, 2C19, 2D6, or 3A4, or induce CYPs 1A2 or 2B6 at the recommended dose of chenodiol of 250 mg TID. Chenodiol and its tauro- conjugate may upregulate CYP3A4 mRNA in vitro. The clinical significance of this upregulation is unknown.

The glyco- and tauro- conjugates of chenodiol are high affinity substrates for BSEP, and in vitro studies suggest that chenodiol may inhibit OATP1B1 and OATP1B3 at the recommended dose of 250 mg TID (clinical significance unknown), but chenodiol and its glyco- and tauro- conjugates are not predicted to inhibit P-gp, BCRP, OATP2B1, OAT1, OAT3, OCT1, OCT2, MATE1, or MATE2-K.

13 NONCLINICAL TOXICOLOGY

13.1 Carcinogenesis, Mutagenesis, Impairment of Fertility

A two-year oral study of chenodiol in rats did not show a carcinogenic potential at the tested levels of 15 to 60 mg/kg/day (0.2 to 0.6 times the recommended human dose based on body surface area). In additional long-term studies, chenodiol given at oral doses up to 600 mg/kg/day in rats (6 times the recommended human dose based on body surface area), and 1000 mg/kg/day in mice (5 times the recommended human dose based on body surface area) induced benign and malignant liver cell tumors in female rats and cholangiomas in female rats and male mice. Two-year studies of lithocholic acid (a major metabolite of chenodiol) in mice (125 to 250 mg/kg/day, equivalent to 0.7 to 1.4 times the recommended human dose based on body surface area) and rats (250 and 500 mg/kg/day, equivalent to 3 to 5 times the recommended human dose based on body surface area) found it not to be carcinogenic. The dietary administration of lithocholic acid to chickens is reported to cause hepatic adenomatous hyperplasia.

13.2 Animal Toxicology and/or Pharmacology

Chenodiol caused hepatobiliary toxicity (e.g., cholestasis) in many animal species, including rodents, non-rodents, and non-human primates at doses close to the human dose. Less efficient sulfation of the chenodiol metabolite, lithocholic acid, in non-human primates compared to humans is thought to cause the hepatobiliary toxicity of orally dosed chenodiol. However, there is evidence that the hepatobiliary toxicity is partly due to the parent drug, chenodiol.

14 CLINICAL STUDIES

The efficacy of CTEXLI for the treatment of patients with CTX was evaluated in Trial 1, which was a randomized, double-blind, placebo controlled, 2-period with 2-treatment crossover trial in patients ≥16 years of age (NCT 04270682).

In Trial 1, 14 patients were enrolled and 13 patients were randomized and treated in a crossover withdrawal design to receive either CTEXLI 250 mg or placebo orally three times daily for 4 weeks during 2 double-blind treatment periods. The study also included treatment with CTEXLI 250 mg three times daily during an 8 week run-in period and an 8-week open label period in between the 2 double-blind withdrawal periods. The total duration of study treatment was 24 weeks.

Of the 13 randomized patients, 62% were male and 39% were female. The baseline median age was 42 years (16-55) and median age at diagnosis was 35 years (15-55). CTEXLI is not approved for use in pediatric patients. The patient population consisted of 62% White, 15% Asian, and 23% Other (In the Other racial group, there was one patient who reported both White and Black). Ethnicity consisted of 15% Hispanic or Latino, 54% not Hispanic or Latino, and 31% unknown.

Plasma cholestanol and urine 23S-pentol were assessed at multiple time points as shown in Figure 1. For plasma cholestanol, the estimated mean change from baseline at day 29 was -2.3 µg/mL when patients continued CTEXLI treatment and 6.2 µg/mL when patients received placebo. The estimated treatment difference was -8.5 µg/mL (95% CI: -13.2, -3.9) (Table 1). For urine 23S-pentol, the estimated mean change from baseline at day 29 was 185 ng/mL when patients continued CTEXLI treatment and 29506 ng/mL when patients received placebo. The estimated treatment difference was -29321 ng/mL (95% CI: -45701, -12941).

Figure 1: Mean (SE) of Observed Plasma Cholestanol by Treatment Sequence (All Randomized Patients)

DB = double-blind. Solid line represents treatment with CTEXLI and dashed line represents treatment with placebo. The mean values of plasma cholestanol at baselines and end of each DB period are annotated in the figure.

Table 1: Summary Results for Plasma Cholestanol and Urine 23S Pentol
Plasma Cholestanol (µg/mL) | Mean (SD) | CTEXLI (N = 13) | Placebo; (N = 13)
Plasma Cholestanol (µg/mL) | Baseline | 10.8 (10.0) | 8.8 (7.8)
Plasma Cholestanol (µg/mL) | Day 29 | 8.5 (7.0) | 15.1 (8.8)
Plasma Cholestanol (µg/mL) | Change from Baseline at Day 29 | -2.3 (3.9) | 6.2 (5.6)
Plasma Cholestanol (µg/mL) | Treatment Difference | -8.5 (95% CI: -13.2, -3.9)
Urine 23S- Pentol (ng/mL) | Baseline | 1811 (1693) | 1773 (1940)
Urine 23S- Pentol (ng/mL) | Day 29 | 1996 (1341) | 31279 (27595)
Urine 23S- Pentol (ng/mL) | Change from Baseline at Day 29 | 185 (1479) | 29506 (27257)
Urine 23S- Pentol (ng/mL) | Treatment Difference | -29321 (95% CI: -45701, -12941)
For each study treatment (placebo or CTEXLI), the mean value at Baseline was calculated as the mean of the measurements obtained prior to receiving the study treatment during the double-blind study duration; and the mean value at Day 29 was calculated as the mean of the measurements at Day 29 at the end of the study treatment.
For each patient at each visit, the measurement of urine 23S-pentol was calculated as the geometric mean of first 3 morning void urine samples collected within 5 days prior to the visit.

16 HOW SUPPLIED/STORAGE AND HANDLING

How Supplied

CTEXLI (chenodiol) tablets are supplied as 250 mg white film-coated tablets imprinted with “MP” on one side and "250" on the other side.

NDC 79378-310-90: 100 count bottle

Storage and Handling

Store CTEXLI at 20°C to 25°C (68°F to 77°F); excursions permitted between 15°C to 30°C (59°F to 86°F) [see USP Controlled Room Temperature].

17 PATIENT COUNSELING INFORMATION

Hepatotoxicity

Inform the patient of the symptoms of hepatotoxicity (e.g., abdominal pain, bruising, dark-colored urine, fatigue, bleeding, jaundice, nausea, and pruritus). Instruct the patient to discontinue CTEXLI immediately and seek medical care should symptoms occur [see Warnings and Precautions (5.1)].

Rx only
Manufactured for:
Mirum Pharmaceuticals, Inc.
Foster City, CA 94404

© 2025 Mirum Pharmaceuticals, Inc.
CTEXLI® is a registered trademark of Mirum Pharmaceuticals, Inc.

PACKAGE/LABEL PRINCIPAL DISPLAY PANEL

QR 2D;
NDC: 79378-310-90;
GTIN: XXXXXXXXXXXXXX;
LOT: XXXXXX;
EXP: YYYY-MM-DD;

NDC 79378-310-90;

Ctexli; (chenodiol); tablets; 250 mg; For oral use; 100 Tablets; Rx only;

Recommended Dosage: see Prescribing Information.

Store at 20°C to 25°C (68°F to 77°F), excursions permitted between 15°C to 30°C (59°F to 86°F) [see USP Controlled Room Temperature].

KEEP THIS AND ALL MEDICATION OUT OF THE REACH OF CHILDREN.

Manufactured for
Mirum Pharmaceuticals, Inc.
Foster City, CA 94404